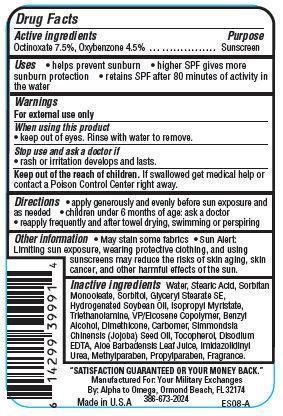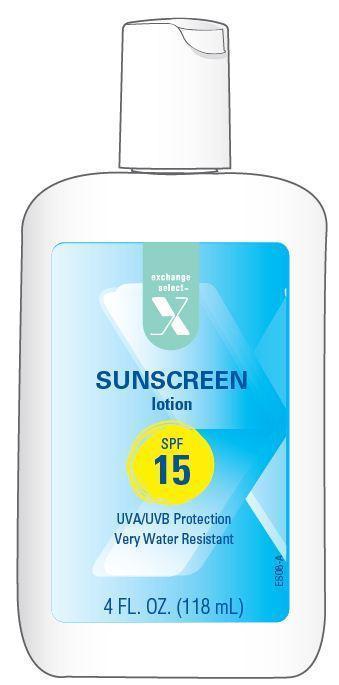 DRUG LABEL: Exchange Select Sunscreen
NDC: 55301-000 | Form: LOTION
Manufacturer: ARMY AND AIR FORCE EXCHANGE SERVICE
Category: otc | Type: HUMAN OTC DRUG LABEL
Date: 20121115

ACTIVE INGREDIENTS: OCTINOXATE 7.5 g/100 g; OXYBENZONE 4.5 g/100 g
INACTIVE INGREDIENTS: WATER; STEARIC ACID; SORBITAN MONOSTEARATE; SORBITOL; GLYCERYL STEARATE SE; HYDROGENATED SOYBEAN OIL; ISOPROPYL MYRISTATE; TROLAMINE; BENZYL ALCOHOL; DIMETHICONE; JOJOBA OIL; TOCOPHEROL; EDETATE DISODIUM; ALOE VERA LEAF; IMIDUREA; METHYLPARABEN; PROPYLPARABEN

Drug Facts

Active ingredients

Octinoxate 7.5%

Oxybenzone 4.5%

Purpose

Sunscreen

Uses

- helps prevent sunburn
- higher SPF gives more sunburn protection
- retains SPF after 80 minutes of activity in the water

Warnings

For external use only

When using this product

- keep out of eyes. Rinse with water to remove.

Stop use and ask a doctor if

- rash or irritation develops and lasts.

Keep Out of the reach of children.

If swallowed get medical help or contact a Poison Control Center right away.

Directions

- apply generously before sun exposure and as needed
- children under 6 months of age:ask a doctor
- reapply frequently and after towel drying, swimming or perspiring.

Other Information

- May stain some fabrics
- Sun Alert: Limiting sun exposure, wearing protective clothing, and using sunscreens may reduce the risks of skin aging, skin cance, and other harmful effects of the sun.

Inactive ingredients

Water, Stearic Acid, Sorbitan Oleate, Sorbitol, Glyceryl Stearate SE, Hydrogenated Soybean Oil, Isopropyl Myristate, Triethanolamine, VP/Eicosene Copolymer, Benzyl Alcohol, Dimethicone, Carbomer, Simmondsia Chinensis (Jojoba) Seed Oil, Tocopherol, Disodium EDTA, Aloe Barbadensis Leaf Juice, Imidazolidinyl Urea, Methylparaben, Propylparaben, Fragrance.

Principal Display Panel

exchange

select

X

SUNSCREEN

Lotion

SPF

15

UVA/UVB Protection

Very Water Resistant

4 FL. OZ. (118 mL)